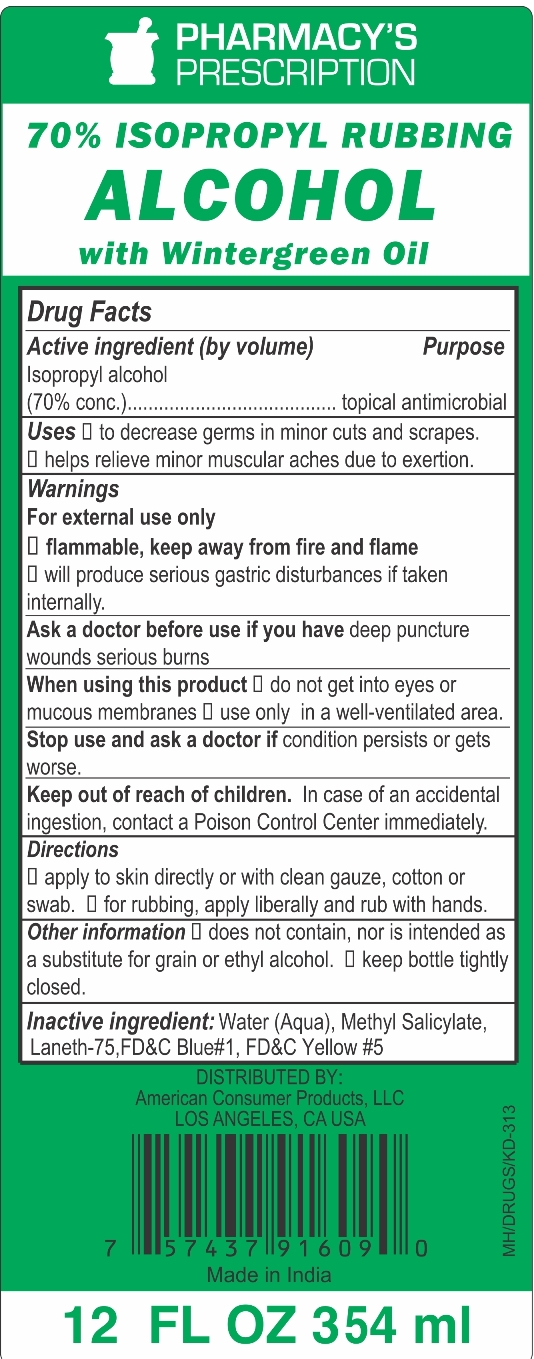 DRUG LABEL: 70% Isopropyl Rubbing Alcohol with Wintergreen
NDC: 18027-005 | Form: LIQUID
Manufacturer: AMERICAN CONSUMER PRODUCTS LLC
Category: otc | Type: HUMAN OTC DRUG LABEL
Date: 20170720

ACTIVE INGREDIENTS: ISOPROPYL ALCOHOL 70 mL/100 mL
INACTIVE INGREDIENTS: WATER; METHYL SALICYLATE; PEG-75 LANOLIN; FD&C BLUE NO. 1; FD&C YELLOW NO. 5

70% Isopropyl Rubbing Alcohol with Wintergreen

Active Ingredient (by volume)

Isopropyl alcohol (70% conc.)

Purpose

Topical Antimicrobial

Uses

- decrease germs in minor cuts and scrapes.
- helps relieve minor muscular aches due to exertion.

Warnings

For external use only

- flammable, keep away from fire and flame
- will produce serious gastric disturbances if taken internally.

Ask a doctor before use if you have deep puncture wounds serious burns

When using this product

- do not get into eyes or mucous membranes
- use only in a well-ventilated area

Stop use and ask a doctor if condition persists or gets worse.

Keep out of reach of children. In case of an accidental ingestion, contact a Poison Control Center immediately.

Directions

- apply to skin directly or with clean gauze, cotton or swab
- for rubbing, apply liberally and rub with hands

Other information

- does not contain, nor is intended as a substitute for grain or ethyl alcohol
- keep bottle tightly closed

Inactive Ingredients

Water (Aqua), Methyl Salicylate, Laneth-75, FD&C Blue #1, FD&C Yellow #5

PACKAGE LABEL

PRINCIPAL DISPLAY PANEL

70% ISOPROPYL RUBBING ALCOHOL WITH WINTERGEEN

Topical Antimicrobial

12 FL.OZ (354 mL)